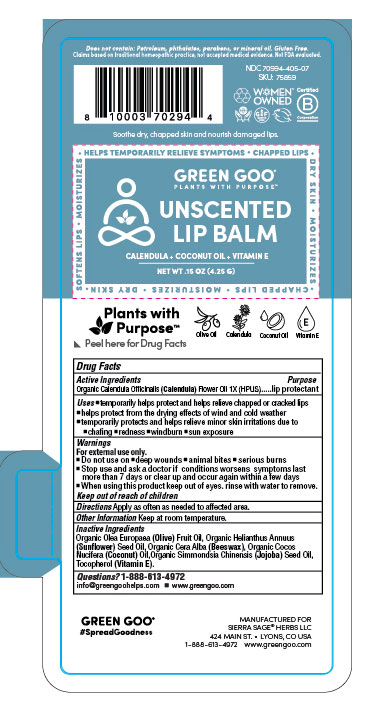 DRUG LABEL: Unscented Lip Balm
NDC: 70994-405 | Form: SALVE
Manufacturer: Sierra Sage Herbs LLC
Category: homeopathic | Type: HUMAN OTC DRUG LABEL
Date: 20220302

ACTIVE INGREDIENTS: CALENDULA OFFICINALIS FLOWER 1 [hp_X]/100 g
INACTIVE INGREDIENTS: OLIVE OIL; JOJOBA OIL; SUNFLOWER OIL; ALPHA-TOCOPHEROL; YELLOW WAX; COCONUT OIL

Unscented Liip Balm

Purpose Section

Skin Protectant

Active Ingredients

Organic Calendula Officinalis (Calendula) Flowers 1X (HPUS)

Indications and Usage

• temporarily helps relieve • chapped or cracked lips

• helps protect from the drying effects of wind and cold weather

•temporarily protects and helps relieve minor skin irritations due to • chaffing • redness • windburn • sun exposure

• temporarily helps moisturize ª chapped and cracked lips

Keep our of Reach of Children

Keep out of reach of children.

Warning Section

Warnings

For external use only.

■ Do not use on ■ deep wounds ■ animal bites ■ serious burns

■ Stop use and ask a doctor if conditions worsens symptoms last more than 7 days or clear up and occur again within a few days

■ When using this product keep out of eyes. rinse with water to remove.

Storange and Handling

Store at room temperature.

Dosage & Administration

Apply as often as needed to affected area.

Inactive Ingredients

Organic Beeswax (Cera alba), Organic Cocos nucifera (Coconut) Oil, Organic Jojoba (Simmondsia Chinensis) Oil, Organic Helianthus annuus (Sunflower) Oil, Organic Olive (Olea europaea) Oil, Tocopherols (Vitamin E) Oil.